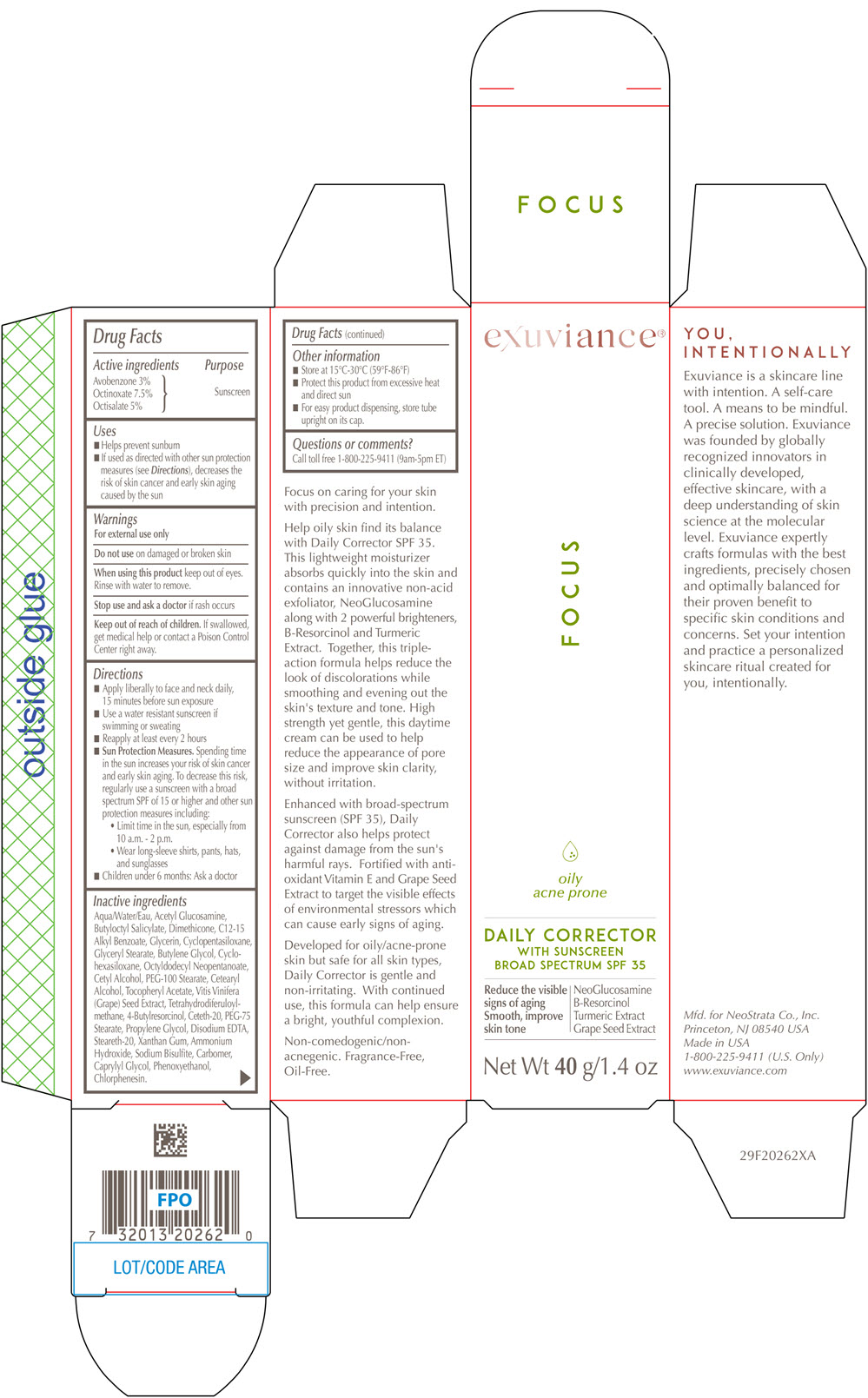 DRUG LABEL: Exuviance Daily Corrector
NDC: 58414-0024 | Form: CREAM
Manufacturer: NeoStrata Company Inc.
Category: otc | Type: HUMAN OTC DRUG LABEL
Date: 20250110

ACTIVE INGREDIENTS: OCTINOXATE 75 mg/1 g; OCTISALATE 50 mg/1 g; AVOBENZONE 30 mg/1 g
INACTIVE INGREDIENTS: WATER; N-ACETYLGLUCOSAMINE; BUTYLOCTYL SALICYLATE; DIMETHICONE; ALKYL (C12-15) BENZOATE; GLYCERIN; CYCLOMETHICONE 5; GLYCERYL MONOSTEARATE; BUTYLENE GLYCOL; CYCLOMETHICONE 6; OCTYLDODECYL NEOPENTANOATE; CETYL ALCOHOL; PEG-100 STEARATE; CETOSTEARYL ALCOHOL; VITIS VINIFERA SEED; .ALPHA.-TOCOPHEROL ACETATE; PROPYLENE GLYCOL; 4-BUTYLRESORCINOL; TETRAHYDRODIFERULOYLMETHANE; PEG-75 STEARATE; STEARETH-20; CETETH-20; XANTHAN GUM; SODIUM BISULFITE; EDETATE DISODIUM ANHYDROUS; AMMONIA; CARBOMER HOMOPOLYMER, UNSPECIFIED TYPE; CAPRYLYL GLYCOL; PHENOXYETHANOL; CHLORPHENESIN

Exuviance®Daily Corrector
with Sunsreen Broad Spectrum SPF 35

Drug Facts

Active ingredients

Avobenzone 3%
Octinoxate 7.5%
Octisalate 5%

Purpose

Sunscreen

Uses

- Helps prevent sunburn
- If used as directed with other sun protection measures (see Directions), decreases the risk of skin cancer and early skin aging caused by the sun

Warnings

For external use only

Do not useon damaged or broken skin

WHEN USING

When using this productkeep out of eyes. Rinse with water to remove.

Stop use and ask a doctorif rash occurs

Keep out of reach of children. If swallowed, get medical help or contact a Poison Control Center right away.

Directions

- Apply liberally to face and neck daily, 15 minutes before sun exposure
- Use a water resistant sunscreen if swimming or sweating
- Reapply at least every 2 hours
- Sun Protection Measures.Spending time in the sun increases your risk of skin cancer and early skin aging. To decrease this risk, regularly use a sunscreen with a broad spectrum SPF of 15 or higher and other sun protection measures including:
  - Limit time in the sun, especially from 10 a.m. – 2 p.m.
  - Wear long-sleeve shirts, pants, hats, and sunglasses
- Children under 6 months: Ask a doctor

Inactive ingredients

Water, Acetyl Glucosamine, Butyloctyl Salicylate, Dimethicone, C12-15 Alkyl Benzoate, Glycerin, Cyclopentasiloxane, Glyceryl Stearate, Butylene Glycol, Cyclohexasiloxane, Octyldodecyl Neopentanoate, Cetyl Alcohol, PEG-100 Stearate, Cetearyl Alcohol, Tocopheryl Acetate, Vitis Vinifera (Grape) Seed Extract, Tetrahydrodiferuloylmethane, 4-Butylresorcinol, Ceteth-20, PEG-75 Stearate, Propylene Glycol, Disodium EDTA, Steareth-20, Xanthan Gum, Ammonium Hydroxide, Sodium Bisulfite, Carbomer, Caprylyl Glycol, Phenoxyethanol, Chlorphenesin,

Other information

- Store at 15°C-30°C (59°F – 86°F)
- Protect this product from excessive heat and direct sun
- For easy product dispensing, store tube upright on its cap.

Questions or comments?

Call toll-free 1-800-225-9411 (9am – 5pm ET)

PRINCIPAL DISPLAY PANEL - 40 g Tube Carton

exuviance®

FOCUS

oily
acne prone
DAILY CORRECTOR
WITH SUNSCREEN
BROAD SPECTRUM SPF 35
Reduce the visible
signs of aging
Smooth, improve
skin tone
NeoGlucosamine
B-Resorcinol
Turmeric Extract
Grape Seed Extract

Net Wt 40 g/1.4 oz